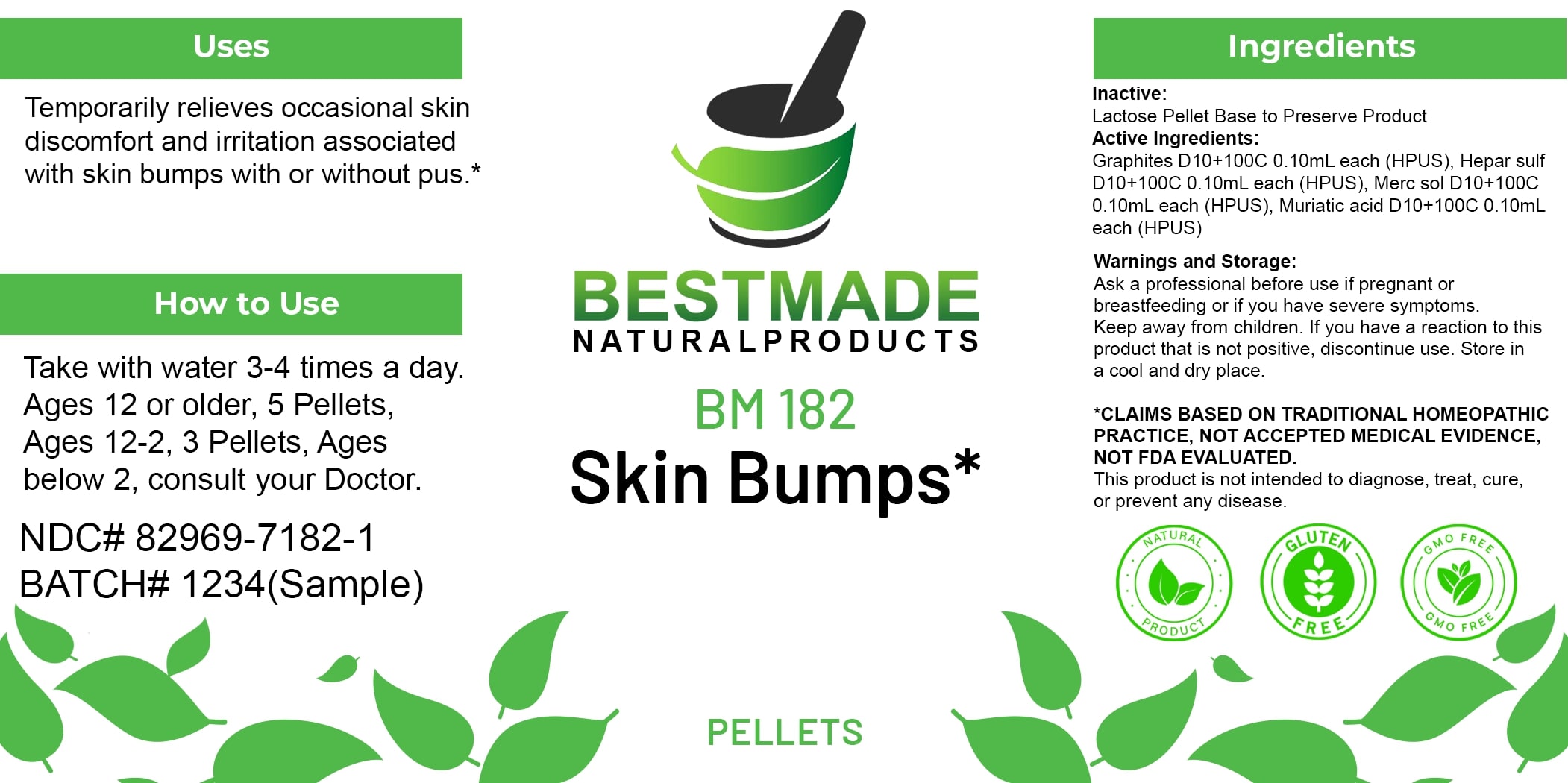 DRUG LABEL: Bestmade Natural Products BM182 Pellets
NDC: 82969-7182 | Form: TABLET, SOLUBLE
Manufacturer: Bestmade Natural Products
Category: homeopathic | Type: HUMAN OTC DRUG LABEL
Date: 20250408

ACTIVE INGREDIENTS: GRAPHITE 30 [hp_C]/30 [hp_C]; CALCIUM SULFIDE 30 [hp_C]/30 [hp_C]; MERCURIUS SOLUBILIS 30 [hp_C]/30 [hp_C]; HYDROCHLORIC ACID 30 [hp_C]/30 [hp_C]
INACTIVE INGREDIENTS: LACTOSE 30 [hp_C]/30 [hp_C]

BM182 Pellets

DOSAGE AND ADMINISTRATION

How to Use

Take with water 3-4 times a day. Ages 12 or older, 5 Pellets, Ages 12-2, 3 Pellets, Ages below 2, consult your Doctor.

INACTIVE INGREDIENT

Ingredients

Inactive: Lactose Pellet Base to Preserve Product

ACTIVE INGREDIENT

Active Ingredients: Graphites D10+100C 0.10ml each (HPUS), Hepar sulf D10+100C 0.10ml each (HPUS), Merc sol D10+100C 0.10ml each (HPUS), Muriatic acid D10+100C 0.10ml each (HPUS)

Uses

Temporarily relieves occasional skin discomfort and irritation associated with skin bumps with or without pus.*

*CLAIMS BASED ON TRADITIONAL HOMEOPATHIC PRACTICE. NOT ACCEPTED MEDICAL EVIDENCE. NOT FDA EVALUATED.

This product is not intended to diagnose, treat, cure, or prevent any disease.

Uses

Temporarily relieves occasional skin discomfort and irritation associated with skin bumps with or without pus.*

*CLAIMS BASED ON TRADITIONAL HOMEOPATHIC PRACTICE. NOT ACCEPTED MEDICAL EVIDENCE. NOT FDA EVALUATED.

This product is not intended to diagnose, treat, cure, or prevent any disease.

KEEP OUT OF REACH OF CHILDREN

Warnings and Storage:

Ask a professional before use if pregnant or breastfeeding or if you have severe symptoms. Keep away from children. If you have a reaction to this product that is not positive, discontinue use. Store in a cool and dry place.

Warnings and Storage:

Ask a professional before use if pregnant or breastfeeding or if you have severe symptoms. Keep away from children. If you have a reaction to this product that is not positive, discontinue use. Store in a cool and dry place.

*CLAIMS BASED ON TRADITIONAL HOMEOPATHIC PRACTICE. NOT ACCEPTED MEDICAL EVIDENCE. NOT FDA EVALUATED.

This product is not intended to diagnose, treat, cure, or prevent any disease.

Entire package label